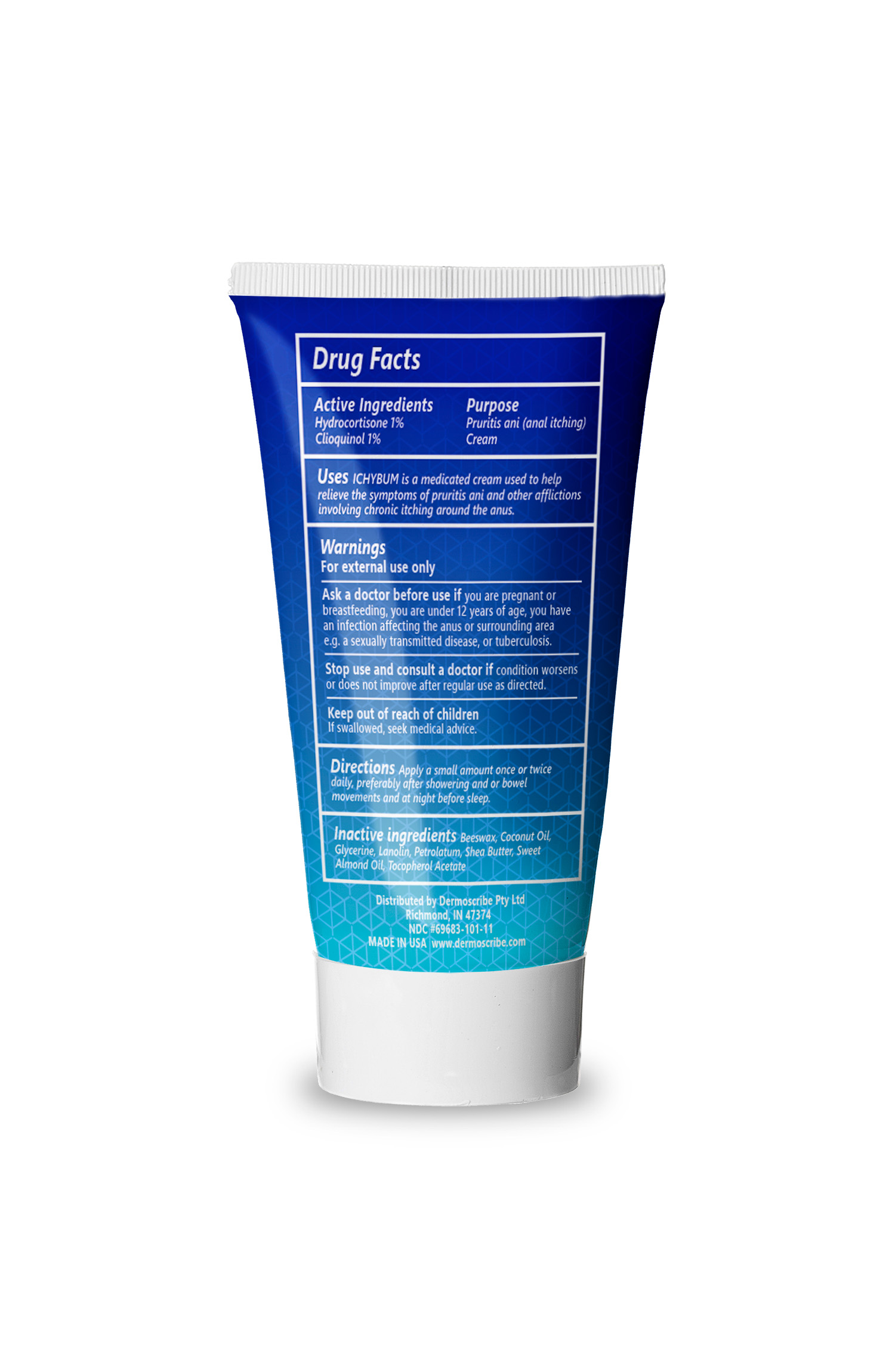 DRUG LABEL: DERMOSCRIBE ICHYBUM
NDC: 69683-101 | Form: CREAM
Manufacturer: DERMOSCRIBE PTY LTD
Category: otc | Type: HUMAN OTC DRUG LABEL
Date: 20251017

ACTIVE INGREDIENTS: HYDROCORTISONE 1 g/100 g; CLIOQUINOL 1 g/100 g
INACTIVE INGREDIENTS: GLYCERIN; LANOLIN; PETROLATUM; BEESWAX; COCONUT OIL; SHEA BUTTER; PRUNUS AMYGDALUS DULCIS (SWEET ALMOND) OIL; ALPHA-TOCOPHEROL ACETATE

DERMOSCRIBE (as PLD) - ICHYBUM CREAM (69683-101)

Active ingredients

HYDROCORTISONE 1%

CLIOQUINOL 1%

Purpose

Pruritis ani (anal itching) cream

Uses

ICHYBUM is a medicated cream used to help relieve the symptoms of pruritis ani and other afflictions involving chronic itching around the anus

Warnings

FOR EXTERNAL USE ONLY

Ask a doctor before use if you are pregnant or breastfeeding, you are under 12 years of age, you have an infection affecting the anus or surrounding area e.e. a sexually transmitted disease, or tuberculosis

Stop use and consult a doctor if condition worsens or does not improve after regular use as directed

KEEP OUT OF REACH OF CHILDREN. If swallowed, seek medical advice

DIRECTIONS

Apply a small amount once or twice daily, preferable after showering and or bowel movements and at night before sleep

INACTIVE INGREDIENTS

Beeswax, Coconut Oil, Glycerine, Lanolin, Petrolatum, Shea Butter, Sweet Almond Oil, Tocopherol Acetate

RECENT MAJOR CHANGES

Updating Drug Facts